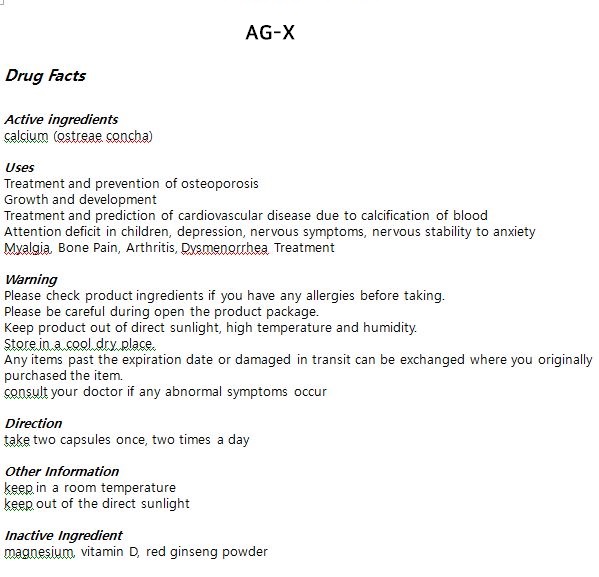 DRUG LABEL: AG-X
NDC: 55259-0007 | Form: TABLET
Manufacturer: APEXEL CO., LTD.
Category: otc | Type: HUMAN OTC DRUG LABEL
Date: 20240220

ACTIVE INGREDIENTS: CALCIUM 0.76 mg/1 1
INACTIVE INGREDIENTS: MAGNESIUM; PANAX GINSENG WHOLE; VITAMIN D

ACTIVE INGREDIENT

calcium

INACTIVE INGREDIENT

magnesium, vitamin D, red ginseng powder

PURPOSE

Treatment and prevention of osteoporosis

Growth and development

Treatment and prediction of cardiovascular disease due to calcification of blood

Attention deficit in children, depression, nervous symptoms, nervous stability to anxiety

Myalgia, Bone Pain, Arthritis, Dysmenorrhea Treatment

KEEP OUT OF REACH OF CHILDREN

WARNING

Please check product ingredients if you have any allergies before taking.

Please be careful during open the product package.

Keep product out of direct sunlight, high temperature and humidity.

Store in a cool dry place.

Any items past the expiration date or damaged in transit can be exchanged where you originally purchased the item.

consult your doctor if any abnormal symptoms occur

USES

for oral use only

INDICATION & USAGE SECTION

take two capsules once, two times a day